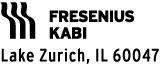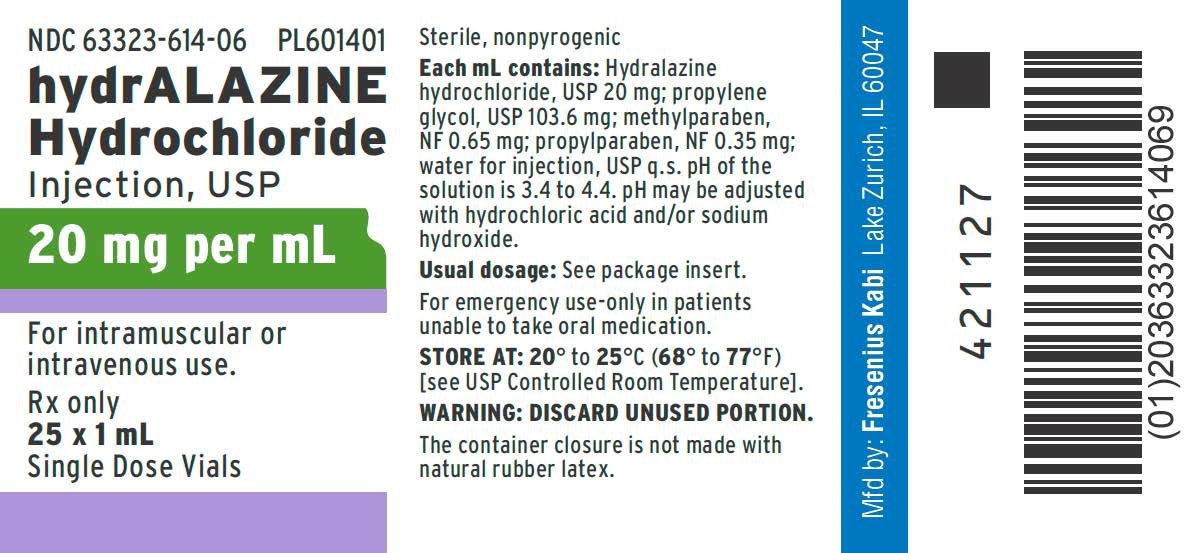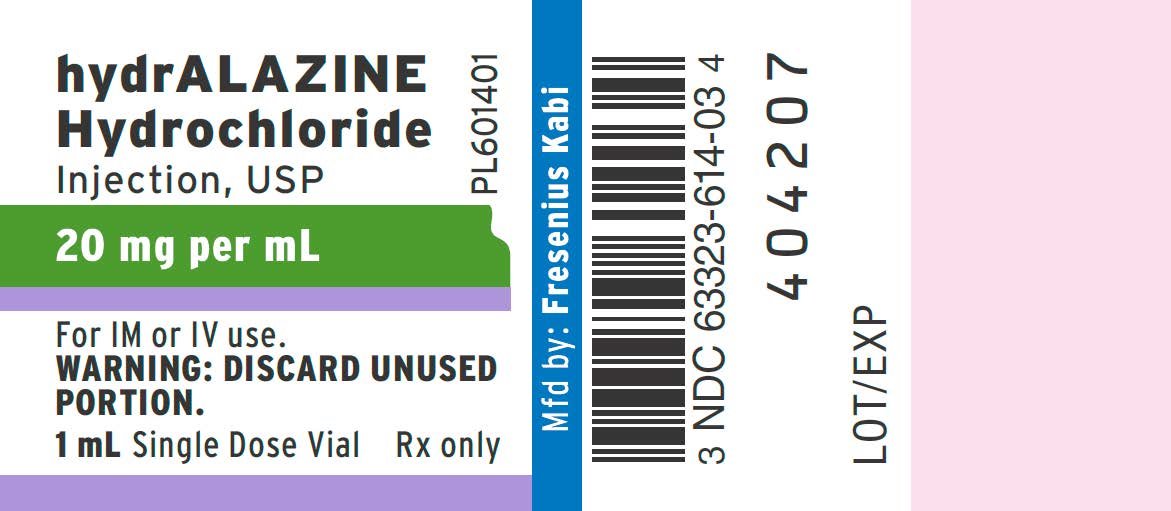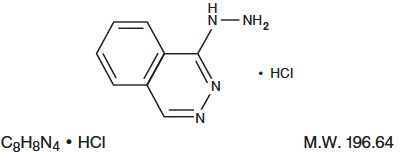 DRUG LABEL: Hydralazine Hydrochloride
NDC: 63323-614 | Form: INJECTION
Manufacturer: Fresenius Kabi USA, LLC
Category: prescription | Type: HUMAN PRESCRIPTION DRUG LABEL
Date: 20251216

ACTIVE INGREDIENTS: HYDRALAZINE HYDROCHLORIDE 20 mg/1 mL
INACTIVE INGREDIENTS: PROPYLENE GLYCOL 103.6 mg/1 mL; METHYLPARABEN 0.65 mg/1 mL; PROPYLPARABEN 0.35 mg/1 mL; HYDROCHLORIC ACID; SODIUM HYDROXIDE

Hydralazine Hydrochloride Injection, USP

DESCRIPTION:

Rx only

Hydralazine Hydrochloride Injection, USP is an antihypertensive available in a 2 mL vial for intravenous and intramuscular administration. Each mL of the sterile, nonpyrogenic colorless solution contains hydralazine hydrochloride USP, 20 mg; methylparaben NF, 0.65 mg; propylparaben NF, 0.35 mg; propylene glycol USP, 103.6 mg, and Water for Injection USP q.s. The pH of the solution is 3.4 to 4.4. pH may be adjusted with hydrochloric acid and/or sodium hydroxide. Hydralazine hydrochloride is 1-hydrazinophthalazine monohydrochloride, and its structural formula is:

Hydralazine hydrochloride USP is a white to off-white, odorless crystalline powder. It is soluble in water, slightly soluble in alcohol, and very slightly soluble in ether. It melts at about 275°C, with decomposition.

CLINICAL PHARMACOLOGY:

Although the precise mechanism of action of hydralazine is not fully understood, the major effects are on the cardiovascular system. Hydralazine apparently lowers blood pressure by exerting a peripheral vasodilating effect through a direct relaxation of vascular smooth muscle. Hydralazine, by altering cellular calcium metabolism, interferes with the calcium movements within the vascular smooth muscle that are responsible for initiating or maintaining the contractile state.

The peripheral vasodilating effect of hydralazine results in decreased arterial blood pressure (diastolic more than systolic); decreased peripheral vascular resistance; and an increased heart rate, stroke volume and cardiac output. The preferential dilatation of arterioles, as compared to veins, minimizes postural hypotension and promotes the increase in cardiac output. Hydralazine usually increases renin activity in plasma presumably as a result of increased secretion of renin by the renal juxtaglomerular cells in response to reflex sympathetic discharge. This increase in renin activity leads to the production of angiotensin II, which then causes stimulation of aldosterone and consequent sodium reabsorption. Hydralazine also maintains or increases renal and cerebral blood flow.

The average maximal decrease in blood pressure usually occurs 10-80 minutes after administration of hydralazine hydrochloride injection. No other pharmacokinetic data on hydralazine hydrochloride injection are available.

INDICATIONS AND USAGE:

Severe essential hypertension when the drug cannot be given orally or when there is an urgent need to lower blood pressure.

CONTRAINDICATIONS:

Hypersensitivity to hydralazine, coronary artery disease, mitral valvular rheumatic heart disease.

WARNINGS:

In a few patients, hydralazine may produce a clinical picture simulating systemic lupus erythematosus including glomerulonephritis. In such patients, hydralazine should be discontinued unless the benefit-to-risk determination requires continued antihypertensive therapy with this drug. Symptoms and signs usually regress when the drug is discontinued but residua have been detected many years later. Long-term treatment with steroids may be necessary (see PRECAUTIONS, Laboratory Tests).

PRECAUTIONS:

General

Myocardial stimulation produced by hydralazine can cause anginal attacks and ECG changes of myocardial ischemia. The drug has been implicated in the production of myocardial infarction. It must, therefore, be used with caution in patients with suspected coronary artery disease.

The “hyperdynamic” circulation caused by hydralazine may accentuate specific cardiovascular inadequacies. For example, hydralazine may increase pulmonary artery pressure in patients with mitral valvular disease. The drug may reduce the pressor responses to epinephrine. Postural hypotension may result from hydralazine but is less common than with ganglionic blocking agents. It should be used with caution in patients with cerebral vascular accidents.

In hypertensive patients with normal kidneys who are treated with hydralazine, there is evidence of increased renal blood flow and a maintenance of glomerular filtration rate. In some instances where control values were below normal, improved renal function has been noted after administration of hydralazine. However, as with any antihypertensive agent, hydralazine should be used with caution in patients with advanced renal damage.

Peripheral neuritis, evidenced by paresthesia, numbness, and tingling, has been observed. Publishing evidence suggests an antipyridoxine effect and that pyridoxine should be added to the regimen if symptoms develop.

Laboratory Tests

Complete blood counts and antinuclear antibody titer determinations are indicated before and periodically during prolonged therapy with hydralazine even though the patient is asymptomatic. These studies are also indicated if the patient develops arthralgia, fever, chest pain, continued malaise or other unexplained signs or symptoms.

A positive antinuclear antibody titer requires that the physician carefully weigh the implications of the test results against the benefits to be derived from antihypertensive therapy with hydralazine hydrochloride.

Blood dyscrasias, consisting of reduction in hemoglobin and red cell count, leukopenia, agranulocytosis, and purpura, have been reported. If such abnormalities develop, therapy should be discontinued.

Drug Interactions

MAO inhibitors should be used with caution in patients receiving hydralazine.

When other potent parenteral antihypertensive drugs, such as diazoxide, are used in combination with hydralazine, patients should be continuously observed for several hours for any excessive fall in blood pressure. Profound hypotensive episodes may occur when diazoxide injection and hydralazine hydrochloride injection are used concomitantly.

Carcinogenesis, Mutagenesis, Impairment of Fertility

In a lifetime study in Swiss albino mice, there was a statistically significant increase in the incidence of lung tumors (adenomas and adenocarcinomas) of both male and female mice given hydralazine continuously in their drinking water at a dosage of about 250 mg/kg per day (about 80 times the maximum recommended human dose). In a 2-year carcinogenicity study of rats given hydralazine by gavage at dose levels of 15, 30 and 60 mg/kg/day (approximately 5 to 20 times the recommended human daily dosage), microscopic examination of the liver revealed a small, but statistically significant increase in benign neoplastic nodules in male and female rats from the high-dose group and in female rats from the intermediate-dose group. Benign interstitial cell tumors of the testes were also significantly increased in male rats from the high-dose group. The tumors observed are common in aged rats and a significantly increased incidence was not observed until 18 months of treatment. Hydralazine was shown to be mutagenic in bacterial systems (Gene Mutation and DNA Repair) and in one of two rats and one rabbit hepatocyte in vitro DNA repair studies. Additional in vivo and in vitro studies using lymphoma cells, germinal cells and fibroblasts from mice, bone marrow cells from Chinese hamsters and fibroblasts from human cell lines did not demonstrate any mutagenic potential for hydralazine.

The extent to which these findings indicate a risk to man is uncertain. While long-term clinical observation has not suggested that human cancer is associated with hydralazine use, epidemiologic studies have so far been insufficient to arrive at any conclusions.

Pregnancy

Teratogenic Effects

Pregnancy Category C

Animal studies indicate that hydralazine is teratogenic in mice at 20-30 times the maximum daily human dose of 200-300 mg and possibly in rabbits at 10-15 times the maximum daily human dose, but that it is nonteratogenic in rats. Teratogenic effects observed were cleft palate and malformations of facial and cranial bones.

There are no adequate and well-controlled studies in pregnant women. Although clinical experience does not include any positive evidence of adverse effects on the human fetus, hydralazine should be used during pregnancy only if the expected benefit justifies the potential risk to the fetus.

Nursing Mothers

It is not known whether this drug is excreted in human milk. Because many drugs are excreted in human milk, caution should be exercised when hydralazine injection is administered to a nursing woman.

Pediatric Use

Safety and effectiveness in pediatric patients have not been established in controlled clinical trials, although there is experience with the use of hydralazine hydrochloride in pediatric patients. The usual recommended parenteral dosage, administered intramuscularly or intravenously, is 1.7-3.5 mg/kg of body weight daily, divided into four to six doses.

ADVERSE REACTIONS:

To report SUSPECTED ADVERSE REACTIONS, contact Fresenius Kabi USA, LLC at 1-800-551-7176 or FDA at 1-800-FDA-1088 or www.fda.gov/medwatch.

Adverse reactions with hydralazine hydrochloride are usually reversible when dosage is reduced. However, in some cases it may be necessary to discontinue the drug.

The following adverse reactions have been observed, but there has not been enough systematic collection of data to support an estimate of their frequency.

Common: Headache, anorexia, nausea, vomiting, diarrhea, palpitations, tachycardia, angina pectoris.

Less Frequent: Digestive-constipation, paralytic ileus.

Cardiovascular - hypotension, paradoxical pressor response, edema.

Respiratory - dyspnea.

Neurologic - peripheral neuritis, evidenced by paresthesia, numbness, and tingling; dizziness; tremors; muscle cramps, psychotic reactions characterized by depression, disorientation, or anxiety.

Genitourinary - difficulty in urination.

Hematologic - blood dyscrasias, consisting of reduction in hemoglobin and red cell count, leukopenia, agranulocytosis, purpura; lymphadenopathy; splenomegaly.

Hypersensitive Reactions - rash, urticaria, pruritis, fever, chills, arthralgia, eosinophilia, and, rarely, hepatitis.

Other - nasal congestion, flushing, lacrimation, conjunctivitis.

OVERDOSAGE:

Acute Toxicity

No deaths due to acute poisoning have been reported.

Highest known dose survived: adults, 10 g orally.

Oral LD50 in rats: 173 and 187 mg/kg.

Signs and symptoms of overdosage include hypotension, tachycardia, headache, and generalized skin flushing.

Complications can include myocardial ischemia and subsequent myocardial infarction, cardiac arrhythmia, and profound shock.

Treatment

There is no specific antidote.

Support of the cardiovascular system is of primary importance. Shock should be treated with plasma expanders. If possible, vasopressors should not be given, but if a vasopressor is required, care should be taken not to precipitate or aggravate cardiac arrhythmia. Tachycardia responds to beta blockers. Digitalization may be necessary, and renal function should be monitored and supported as required.

No experience has been reported with extracorporeal or peritoneal dialysis.

DOSAGE AND ADMINISTRATION:

When there is urgent need, therapy in the hospitalized patient may be initiated intramuscularly or as a rapid intravenous bolus injection directly into the vein. Hydralazine Hydrochloride Injection should be used only when the drug cannot be given orally. The usual dose is 20-40 mg, repeated as necessary.

Certain patients (especially those with marked renal damage) may require a lower dose. Blood pressure should be checked frequently. It may begin to fall within a few minutes after injection, with the average maximal decrease occurring in 10-80 minutes. In cases where there has been increased intracranial pressure, lowering the blood pressure may increase cerebral ischemia. Most patients can be transferred to oral hydralazine hydrochloride within 24-48 hours.

The product should be used immediately after the vial is opened. The product should not be added to infusion solutions. Hydralazine Hydrochloride Injection may discolor upon contact with metal; discolored solutions should be discarded.

Parenteral drug products should be inspected visually for particulate matter and discoloration prior to administration, whenever solution and container permit.

HOW SUPPLIED:

Product Code | Unit of Sale | Strength | Each
PL601401 | NDC 63323-614-06 Unit of 25 | 20 mg per mL, 1 mL fill | NDC 63323-614-03 1 mL fill in a 2 mL Single Dose Vial

The container closure is not made with natural rubber latex.

Store at 20° to 25°C (68° to 77°F) [see USP Controlled Room Temperature].

Manufactured by:

www.fresenius-kabi.com/us
451864
Issued: October 2025

PACKAGE LABEL

PACKAGE LABEL - PRINCIPAL DISPLAY - Hydralazine 1 mL Single Dose Tray Label

NDC 63323-614-06 PL601401

hydrALAZINE Hydrochloride
Injection, USP

20 mg per mL

For intramuscular or intravenous use.
Rx only
25 X 1 mL
Single Dose Vials

PACKAGE LABEL

PACKAGE LABEL - PRINCIPAL DISPLAY - Hydralazine 1 mL Single Dose Vial Label

hydrALAZINE Hydrochloride
Injection, USP
PL601401

20 mg per mL

For IM or IV use.
WARNING: DISCARD UNUSED
PORTION
1 mL Single Dose Vial Rx only